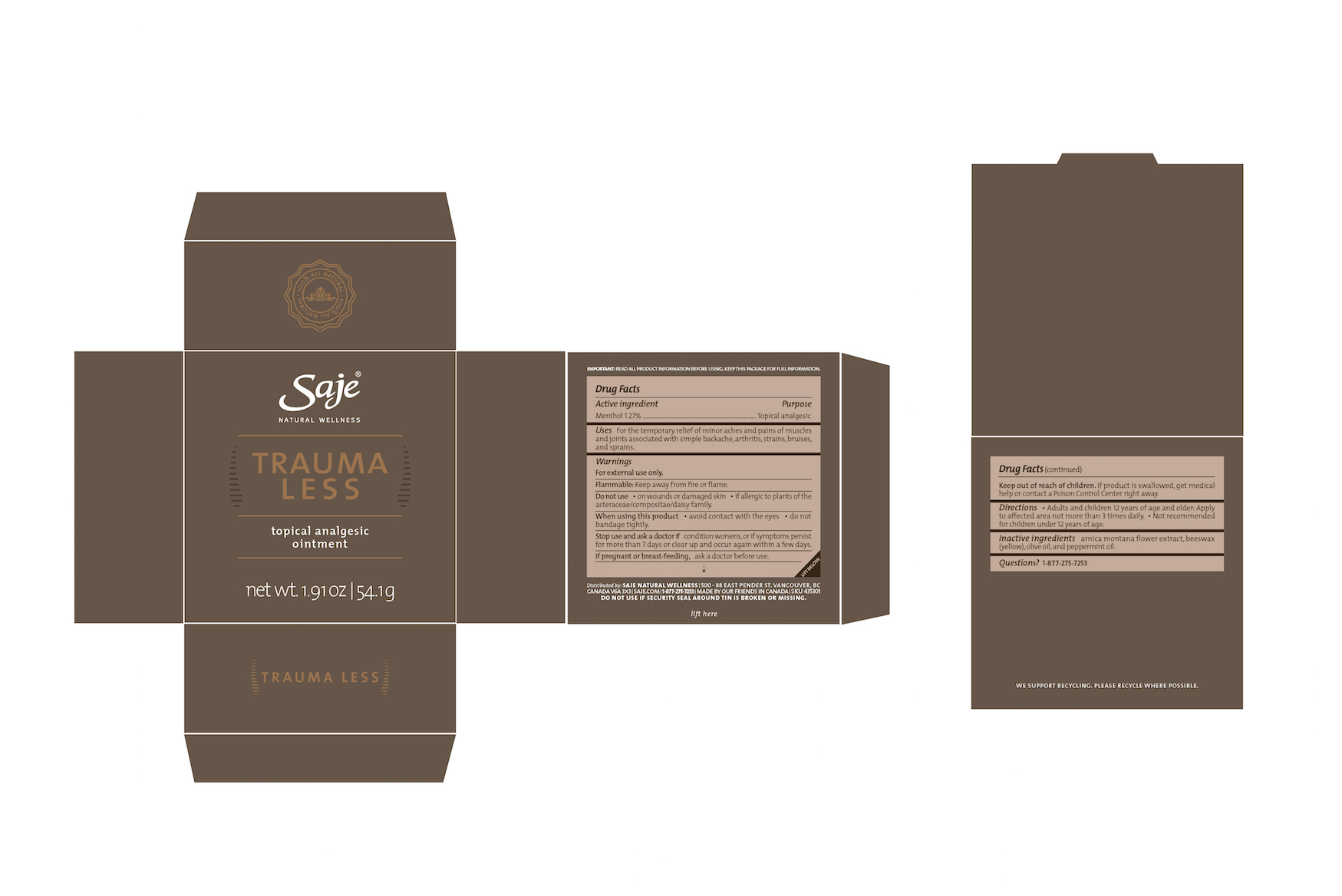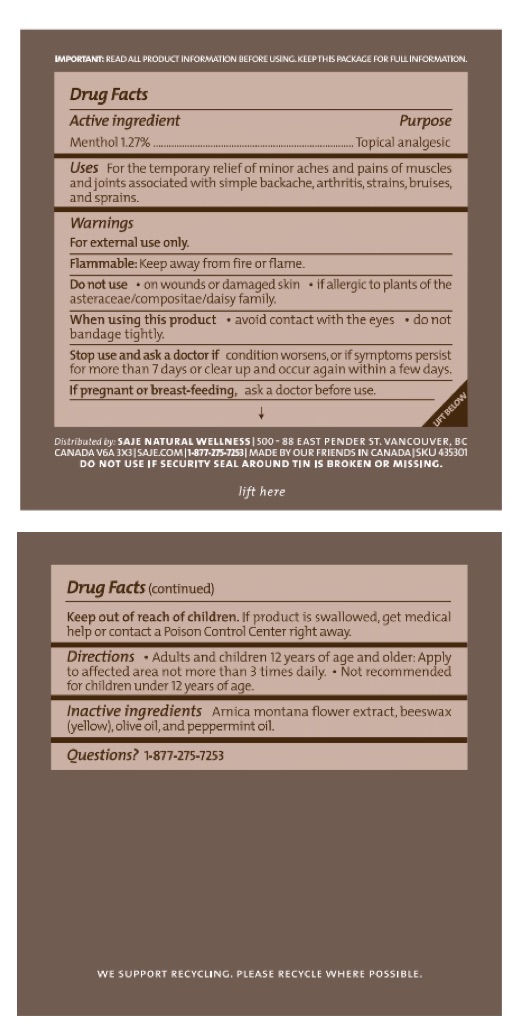 DRUG LABEL: Trauma Less
NDC: 70983-009 | Form: OINTMENT
Manufacturer: Saje Natural Business Inc.
Category: otc | Type: HUMAN OTC DRUG LABEL
Date: 20260112

ACTIVE INGREDIENTS: MENTHOL 12.7 mg/1 g
INACTIVE INGREDIENTS: ARNICA MONTANA FLOWER; YELLOW WAX; OLIVE OIL; PEPPERMINT OIL

Trauma Less Topical Analgesic Ointment

IMPORTANT: READ ALL PRODUCT INFORMATION BEFORE USING. KEEP THIS PACKAGE FOR FULL INFORMATION.

DRUG FACTS Active ingredient

Menthol 1.27%

Purpose Topical Analgesic

Uses For the temporary relief of minor aches and pains of muscles and joints associated with simple backache, arthritis, strains, bruises, and sprains

Warnings

For external use only.

Flammable: Keep away from fire or flame.

Do not use

- on wounds or damaged skin
- if allergic to plants of the asteraceae/compositae/daisy family.

When using this product

- avoid contact with the eyes
- do not bandage tightly

Stop use and ask a doctor if

condition worsens, or if symptoms persist for more than 7 days or clear up and occur again within a few days.

If pregnant or breast-feeding,

ask a doctor before use.

Keep out of reach of children.

If product is swallowed, get medical help or contact a Poison Control Center right away.

Directions

- Adults and children 12 years of age and older: Apply to affected area

DOSAGE AND ADMINISTRATION

not more than 3 times daily.

- Not recommended for children under 12 years of age.

Inactive ingredients

Arnica montana flower extract, beeswax (yellow), olive oil, and peppermint oil.

Questions?

1-877-275-7253

Distributed by: SAJE NATURAL WELLNESS 500-88 E. Pender St. Vancouver, BC Canada V6A 3X3 | saje.com | 1-877-275-7253 | Made by our friends in Canada

DO NOT USE IF SECURITY SEAL AROUND TIN IS BROKEN OR MISSING.

SKU 435301

Lift Here

DISPOSAL AND WASTE HANDLING

We support recycling. Please recycle where possible.

Trauma Less Topical Analgesic Ointment

Saje® Natural Wellness

Trauma Less

Topical Analgesic Ointment

net wt. 1.91 oz | 54.1 g and net wt. 0.47 oz | 13.5 g